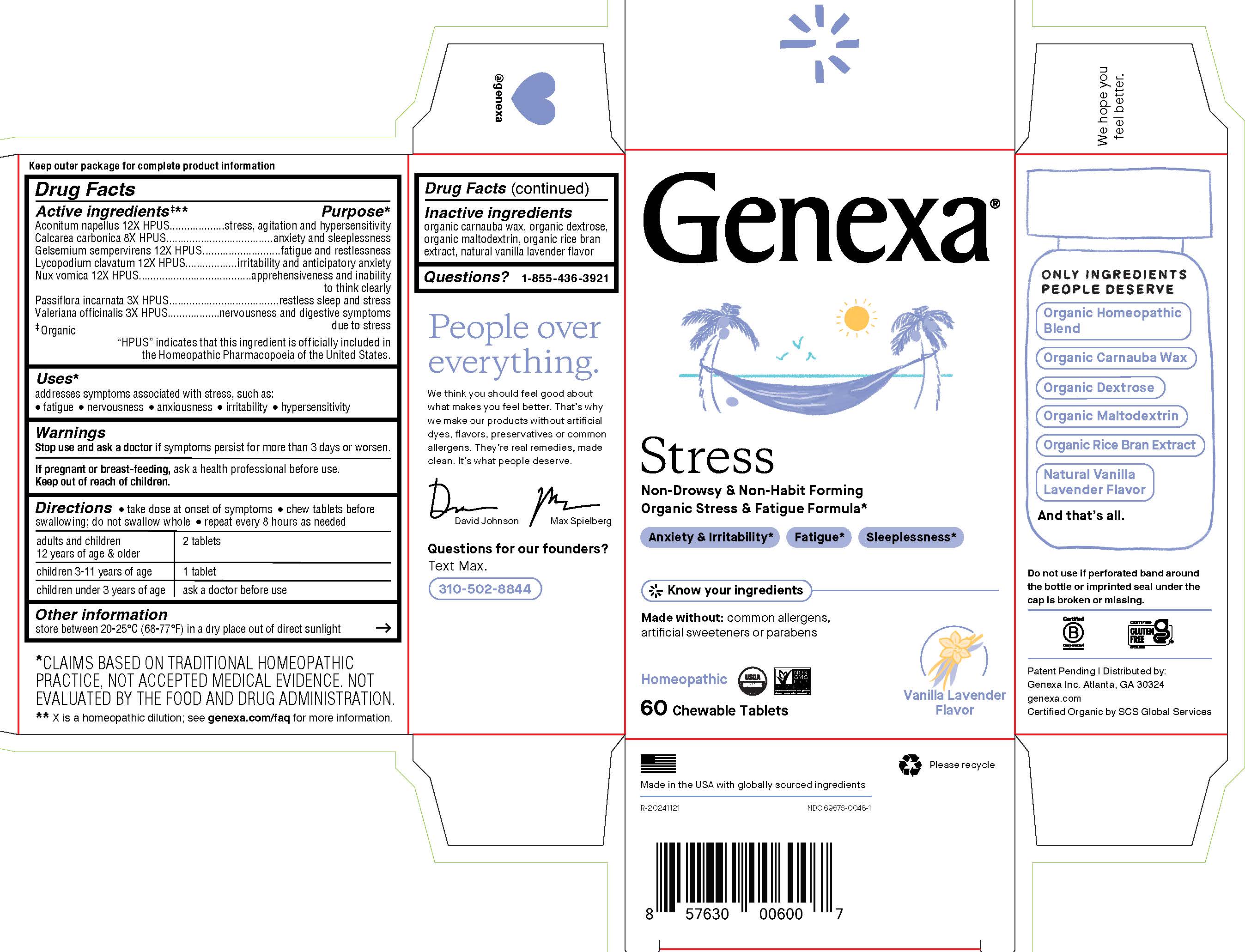 DRUG LABEL: Genexa Stress
NDC: 69676-0048 | Form: TABLET, CHEWABLE
Manufacturer: Genexa Inc.
Category: homeopathic | Type: HUMAN OTC DRUG LABEL
Date: 20250402

ACTIVE INGREDIENTS: STRYCHNOS NUX-VOMICA SEED 12 [hp_X]/1 1; VALERIAN 3 [hp_X]/1 1; ACONITUM NAPELLUS 12 [hp_X]/1 1; OYSTER SHELL CALCIUM CARBONATE, CRUDE 8 [hp_X]/1 1; LYCOPODIUM CLAVATUM SPORE 12 [hp_X]/1 1; PASSIFLORA INCARNATA FLOWERING TOP 3 [hp_X]/1 1; GELSEMIUM SEMPERVIRENS ROOT 12 [hp_X]/1 1
INACTIVE INGREDIENTS: MALTODEXTRIN; DEXTROSE; RICE BRAN; CARNAUBA WAX

STRESS

Drug Facts

Active ingredients‡**

Aconitum napellus 12X HPUS

Calcarea carbonica 8X HPUS

Gelsemium sempervirens 12X HPUS

Lycopodium clavatum 12X HPUS

Nux vomica 12X HPUS

Passiflora incarnata 3X HPUS

Valeriana officinalis 3X HPUS

‡ Organic

"HPUS" indicates that this ingredient is officially included in the Homeopathic Pharmacopoeia of the United States.

Purpose*

stress, agitation and hypersensitivity

anxiety and sleeplessness

fatigue and restlessness

irritability and anticipatory anxiety

apprehensiveness and inability to think clearly

restless sleep and stress

nervousness & digestive symptoms due to stress

Uses*

address symptoms associated with stress, such as:

- fatigue
- nervousness
- anxiousness
- irritability
- hypersensitivity

Warnings

Stop use and ask a doctor if symptoms persist for more than 3 days or worsen.

PREGNANCY OR BREAST FEEDING

If pregnant or breast-feeding, ask a health professional before use.

Keep out of reach of children.

Directions

- take dose at onset of symptoms
- chew tablets before swallowing; do not swallow whole
- repeat every 8 hours as needed

adults and children 12 years of age; and older | 2 tablets
children 3-11 years of age | 1 tablet
children under 3 years of age | ask a doctor before use

Other information

store between 20-25° C (68-77° F) in a dry place out of direct sunlight

Inactive ingredients

organic carnauba wax, organic dextrose, organic maltodextrin, organic rice bran extract, natural vanilla lavender flavor

Questions?

1-855-436-3921

*CLAIMS BASED ON TRADITIONAL HOMEOPATHIC PRACTICE, NOT ACCEPTED MEDICAL EVIDENCE. NOT EVALUATED BY THE FOOD AND DRUG ADMINSTRATION.
** X is a homeopathic dilution; see genexa.com/faq for more information.

Do not use if perforated band around the bottle or imprinted seal under the cap is broken or missing.

Patent Pending | Distributed by:

Genexa Inc. Atlanta, GA 30324

genexa.com

Certified Organic by SCS Global Services

Made in the USA with globally sourced ingredients.

NDC 69676-0048-1

Directions

- take dose at onset of symptoms
- chew tablets before swallowing; do not swallow whole
- repeat every 8 hours as needed

adults and children 12 years of age & older | 2 tablets
children 3-11 years of age | 1 tablet
children under 3 years of age | ask a doctor before use

PACKAGE LABEL

Genexa®

Stress

Non-Drowsy and Non-Habit Forming

Organic Stress & Fatigue Formula*

Anxiety & Irritabilty*

Fatigue*

Sleeplessness*

Know your ingredients

Made without: common allergens, artificial dyes, or parabens

Homeopathic

60 Chewable Tablets

Vanilla Lavender Flavor